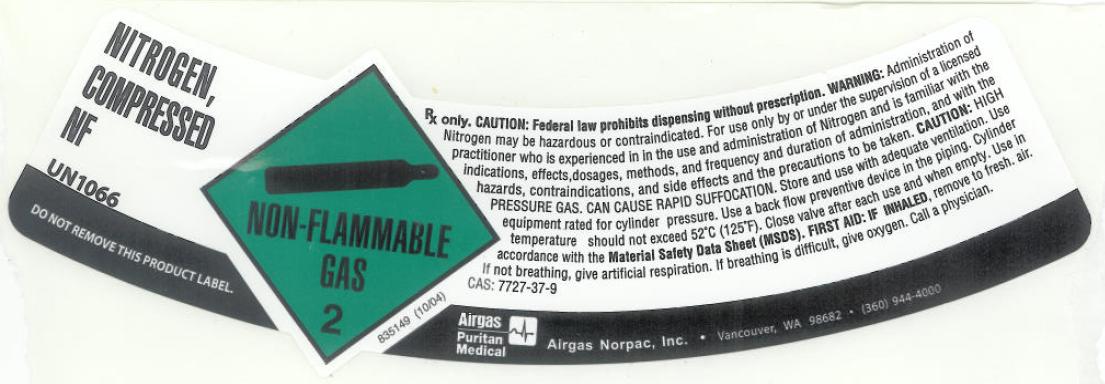 DRUG LABEL: Nitrogen
NDC: 57472-002 | Form: GAS
Manufacturer: AIRGAS NOR PAC INC
Category: prescription | Type: HUMAN PRESCRIPTION DRUG LABEL
Date: 20110506

ACTIVE INGREDIENTS: Nitrogen 995 mL/1 L

nitrogen

PACKAGE LABEL

NITROGEN, COMPRESSED NF UN1066
DO NOT REMOVE THIS PRODUCT LABEL. NON-FLAMMABLE GAS 2 835149 (10/04)
Rx only. CAUTION: Federal law prohibits dispensing without prescription. WARNING: Administration of Nitrogen may be
hazardous or contraindicated. For use only by or under supervision of a licensed practitioner who is experienced in the use
and administration of Nitrogen and is familiar with the indications, effects, dosages, methods, and frequency and duration
of administration, and with the hazards, contraindications, and side effects and the precautions to be taken. CAUTION: HIGH
PRESSURE GAS. CAN CAUSE RAPID SUFFOCATION. Store and use with adequate ventilation. Use equipment rated for cylinder
pressure. Use a back flow preventive device in the piping. Cylinder temperatures should not exceed 52C (125F). Close valve
after each use and when empty. Use in accordance with the Material Safety Data Sheet (MSDS). FIRST AID: IF INHALED, remove
to fresh air. If not breathing, give artificial respiration. If breathing is difficult, give oxygen. Call a physician.
CAS: 7727-37-9
AIRGAS PURITAN MEDICAL Airgas Norpac, Inc. Vancouver, WA 98682 (360) 944-4000